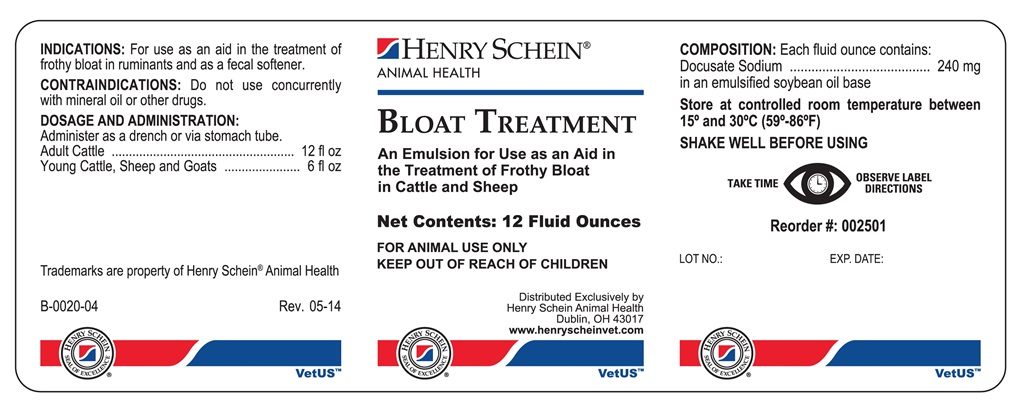 DRUG LABEL: BLOAT TREATMENT
NDC: 11695-4103 | Form: EMULSION
Manufacturer: Henry Schein Animal Health
Category: animal | Type: OTC ANIMAL DRUG LABEL
Date: 20180329

ACTIVE INGREDIENTS: DOCUSATE SODIUM 240 mg/29.57 mL

BLOAT TREATMENT

INDICATIONS AND USAGE

An Emulsion for Use as an Aid in the Treatment of Frothy Bloat in Cattle and Sheep

FOR ANIMAL USE ONLY

KEEP OUT OF REACH OF CHILDREN

INDICATIONS:

For use as an aid in the treatment of frothy bloat in ruminants and as a fecal softener.

CONTRAINDICATIONS

Do not use concurrently with mineral oil or other drugs.

DOSAGE AND ADMINISTRATION

Administer as a drench or via stomach tube.

Adult Cattle ...................................... 12 fl oz
Young Cattle, Sheep and Goats ......... 6 fl oz

COMPOSITION

Each fluid ounce contains:

Docusate Sodium ........................ 240 mg
in an emulsified soybean oil base

STORAGE AND HANDLING

Store at controlled room temperature between 15o and 30oC (59o-86oF)

SHAKE WELL BEFORE USING

TAKE TIME OBSERVE LABEL DIRECTIONS